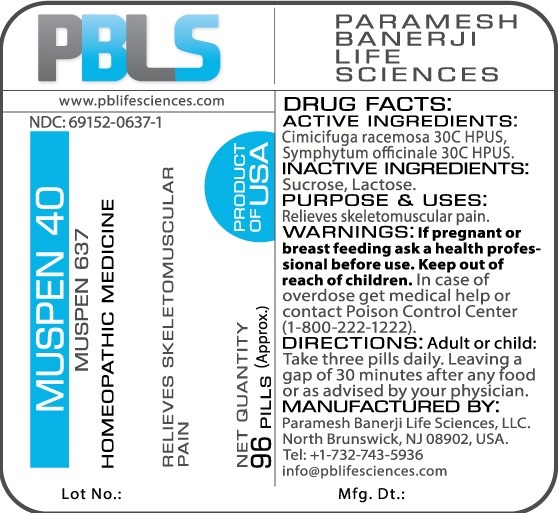 DRUG LABEL: Muspen 40 Number 637
NDC: 69152-0637 | Form: PELLET
Manufacturer: Paramesh Banerji Life Sciences LLC
Category: homeopathic | Type: HUMAN OTC DRUG LABEL
Date: 20160518

ACTIVE INGREDIENTS: BLACK COHOSH 30 [hp_C]/1 1; COMFREY ROOT 30 [hp_C]/1 1
INACTIVE INGREDIENTS: SUCROSE; LACTOSE

DRUG FACTS: Active Ingredients

Cimicifuga racemosa 30C HPUS, Symphytum officinale 30C HPUS

Inactive Ingredients

Sucrose, Lactose

Purpose

Relieves skeletomuscular pain

Uses

Relieves skeletomuscular pain

Warnings

If pregnant or breast feeding ask a health professional before use.

Keep out of reach of children. In case of overdose, get medical help or contact a Poison Control Center (1-800-222-1222) right away.

Direction

Adult or child: Take three pills daily. Leaving a gap of 30 minutes after any food or as advised by your physician.

Manufactured by

Paramesh Banerji Life Sciences, LLC.

North Brunswick, NJ 08902, USA.

Tel: +1-732-743-5936

info@pblifesciences.com

Principal Display Panel

NDC: 69152-0637-1

Muspen 40

Number 637

Homeopathic Medicine

Relieves skeletomuscular pain

Net Quantity

96 Pills (Approx.)

Product of USA